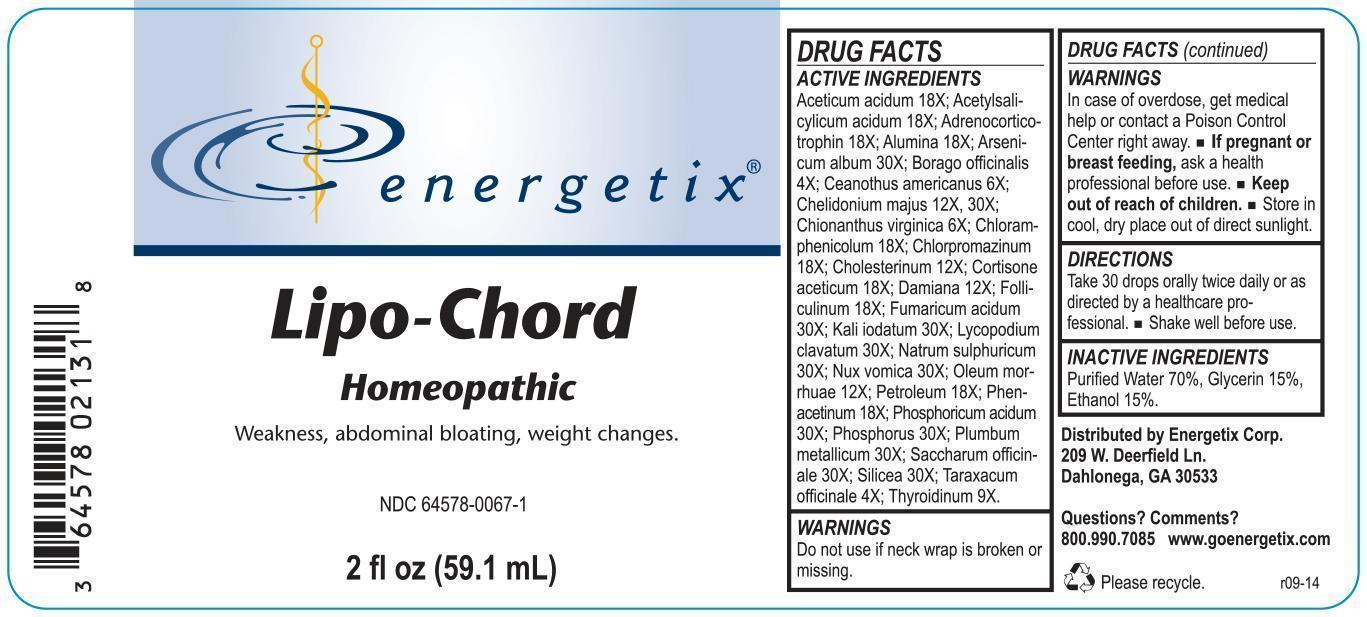 DRUG LABEL: Lipo-Chord
NDC: 64578-0067 | Form: LIQUID
Manufacturer: Energetix Corp
Category: homeopathic | Type: HUMAN OTC DRUG LABEL
Date: 20140619

ACTIVE INGREDIENTS: ACETIC ACID 18 [hp_X]/59.1 mL; ASPIRIN 18 [hp_X]/59.1 mL; CORTICOTROPIN HUMAN 18 [hp_X]/59.1 mL; ALUMINUM OXIDE 18 [hp_X]/59.1 mL; ARSENIC TRIOXIDE 30 [hp_X]/59.1 mL; BORAGE 4 [hp_X]/59.1 mL; CEANOTHUS AMERICANUS LEAF 6 [hp_X]/59.1 mL; CHELIDONIUM MAJUS 12 [hp_X]/59.1 mL; CHIONANTHUS VIRGINICUS BARK 6 [hp_X]/59.1 mL; CHLORAMPHENICOL 18 [hp_X]/59.1 mL; CHLORPROMAZINE 18 [hp_X]/59.1 mL; CHOLESTEROL 12 [hp_X]/59.1 mL; CORTISONE ACETATE 18 [hp_X]/59.1 mL; TURNERA DIFFUSA LEAFY TWIG 12 [hp_X]/59.1 mL; ESTRONE 18 [hp_X]/59.1 mL; FUMARIC ACID 30 [hp_X]/59.1 mL; POTASSIUM IODIDE 30 [hp_X]/59.1 mL; LYCOPODIUM CLAVATUM SPORE 30 [hp_X]/59.1 mL; SODIUM SULFATE 30 [hp_X]/59.1 mL; STRYCHNOS NUX-VOMICA SEED 30 [hp_X]/59.1 mL; COD LIVER OIL 12 [hp_X]/59.1 mL; KEROSENE 18 [hp_X]/59.1 mL; PHENACETIN 18 [hp_X]/59.1 mL; PHOSPHORIC ACID 30 [hp_X]/59.1 mL; PHOSPHORUS 30 [hp_X]/59.1 mL; LEAD 30 [hp_X]/59.1 mL; SUCROSE 30 [hp_X]/59.1 mL; SILICON DIOXIDE 30 [hp_X]/59.1 mL; TARAXACUM OFFICINALE 4 [hp_X]/59.1 mL; THYROID, UNSPECIFIED 9 [hp_X]/59.1 mL
INACTIVE INGREDIENTS: WATER 41.363 mL/59.1 mL; GLYCERIN 8.863 mL/59.1 mL; ALCOHOL 8.863 mL/59.1 mL

Lipo-Chord

ACTIVE INGREDIENT

Aceticum acidum 18X; Acetylsalicylicum acidum 18X; Adrenocorticotrophin 18X; Alumina 18X; Arsenicum album 30X; Borago officinalis 4X; Ceanothus americanus 6X; Chelidonium majus 12X, 30X; Chionanthus virginica 6X; Chloramphenicolum 18X; Chlorpromazinum 18X; Cholesterinum 12X; Cortisone aceticum 18X; Damiana 12X; Folliculinum 18X; Fumaricum acidum 30X; Kali iodatum 30X; Lycopodium clavatum 30X; Natrum sulphuricum 30X; Nux vomica 30X; Oleum morrhuae 12X; Petroleum 18X; Phenacetinum 18X; Phosphoricum acidum 30X; Phosphorus 30X; Plumbum metallicum 30X; Saccharum officinale 30X; Silicea 30X; Taraxacum officinale 4X; Thyroidinum 9X.

Do not use if neck wrap is broken or missing.

OVERDOSAGE

In case of overdose, get medical help or contact a Poison Control Center right away.

PREGNANCY OR BREAST FEEDING

If pregnant or breast feeding, ask a health professional before use.

Keep out of reach of children.

STORAGE AND HANDLING

Store in cool, dry place out of direct sunlight.

Questions? Comments?
800.990.7085 www.goenergetix.com

PURPOSE

Weakness, abdominal bloating, weight changes.

INACTIVE INGREDIENT

Purified Water 70%, Glycerin 15%, Ethanol 15%.

DOSAGE AND ADMINISTRATION

Take 30 drops orally twice daily or as directed by a healthcare professional. Shake well before use.

INDICATIONS AND USAGE

Weakness, abdominal bloating, weight changes.